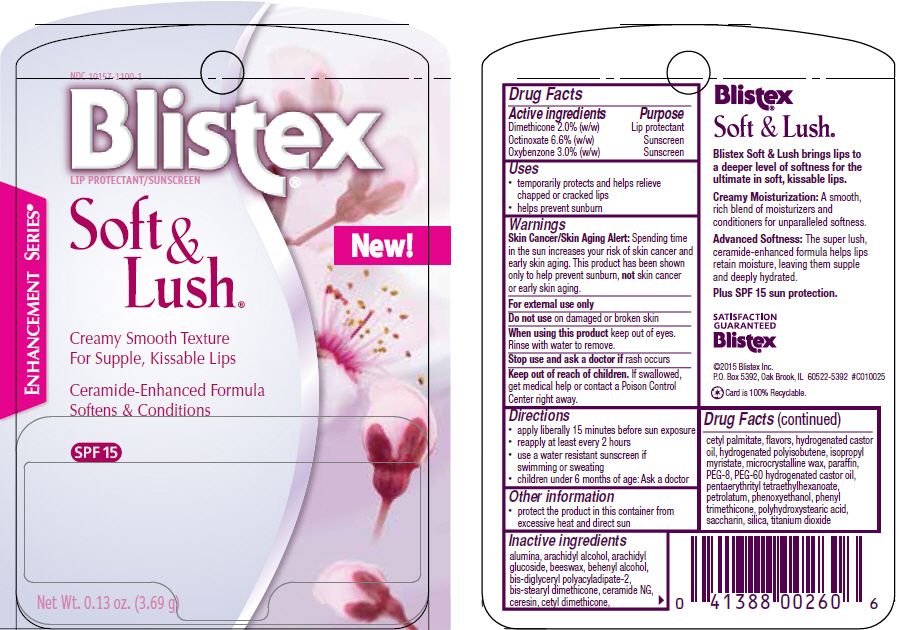 DRUG LABEL: Blistex Soft and Lush
NDC: 10157-1100 | Form: STICK
Manufacturer: Blistex Inc.
Category: otc | Type: HUMAN OTC DRUG LABEL
Date: 20150330

ACTIVE INGREDIENTS: Dimethicone 2 g/100 g; Octinoxate 6.6 g/100 g; Oxybenzone 3 g/100 g
INACTIVE INGREDIENTS: PENTAERYTHRITYL TETRAETHYLHEXANOATE; HYDROGENATED POLYBUTENE (1300 MW); PETROLATUM; MICROCRYSTALLINE WAX; PARAFFIN; PHENYL TRIMETHICONE; HYDROGENATED CASTOR OIL; ISOPROPYL MYRISTATE; TITANIUM DIOXIDE; ALUMINUM OXIDE; SILICON DIOXIDE; YELLOW WAX; CERESIN; CETYL PALMITATE; ARACHIDYL ALCOHOL; DOCOSANOL; ARACHIDYL GLUCOSIDE; CERAMIDE 2; PHENOXYETHANOL; SACCHARIN; POLYHYDROXYSTEARIC ACID (2300 MW); PEG-60 HYDROGENATED CASTOR OIL; POLYETHYLENE GLYCOL 400; CETYL DIMETHICONE 150; STEARYL DIMETHICONE (400 MPA.S AT 50C)

Blistex® Soft and Lush®

Drug Facts

ACTIVE INGREDIENT

Active ingredients | Purpose
Dimethicone 2.0% (w/w) | Lip protectant
Octinoxate 6.6% (w/w) | Sunscreen
Oxybenzone 3.0% (w/w) | Sunscreen

Uses

- temporarily protects and helps relieve chapped or cracked lips
- helps prevent sunburn

Warnings

Skin Cancer/Skin Aging Alert

Spending time in the sun increases your risk of skin cancer and early skin aging. This product has been shown only to help prevent sunburn, not skin cancer or early skin aging.

For external use only

Do not use on damaged or broken skin

When using this product keep out of eyes. Rinse with water to remove.

Stop use and ask a doctor if rash occurs

Keep out of reach of children. If swallowed, get medical help or contact a Poison Control Center right away.

Directions

- apply liberally 15 minutes before sun exposure
- reapply at least every 2 hours
- use a water resistant sunscreen if swimming or sweating
- children under 6 months of age: Ask a doctor

Other information

- protect the product in this container from excessive heat and direct sun

Inactive ingredients

alumina, arachidyl alcohol, arachidyl glucoside, beeswax, behenyl alcohol, bis-diglyceryl polyacyladipate-2, bis-stearyl dimethicone, ceramide NG, ceresin, cetyl dimethicone, cetyl palmitate, flavors, hydrogenated castor oil, hydrogenated polyisobutene, isopropyl myristate, microcrystalline wax, paraffin, PEG-8, PEG-60 hydrogenated castor oil, pentaerythrityl tetraethylhexanoate, petrolatum, phenoxyethanol, phenyl trimethicone, polyhydroxystearic acid, saccharin, silica, titanium dioxide

PRINCIPAL DISPLAY PANEL - 3.69 g Cylinder Blister Pack

NDC 10157-1100-1

Blistex®

LIP PROTECTANT/SUNSCREEN

ENHANCEMENT SERIES®

Soft &
Lush®

New!

Creamy Smooth Texture
For Supple, Kissable Lips

Ceramide-Enhanced Formula
Softens & Conditions

SPF 15

Net Wt. 0.13 oz. (3.69 g)